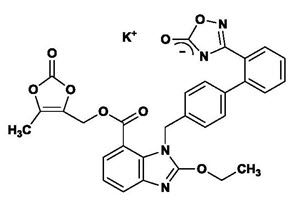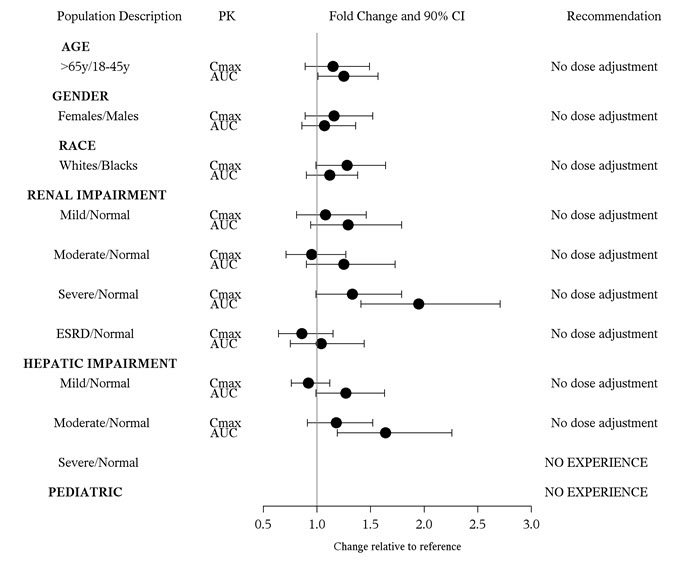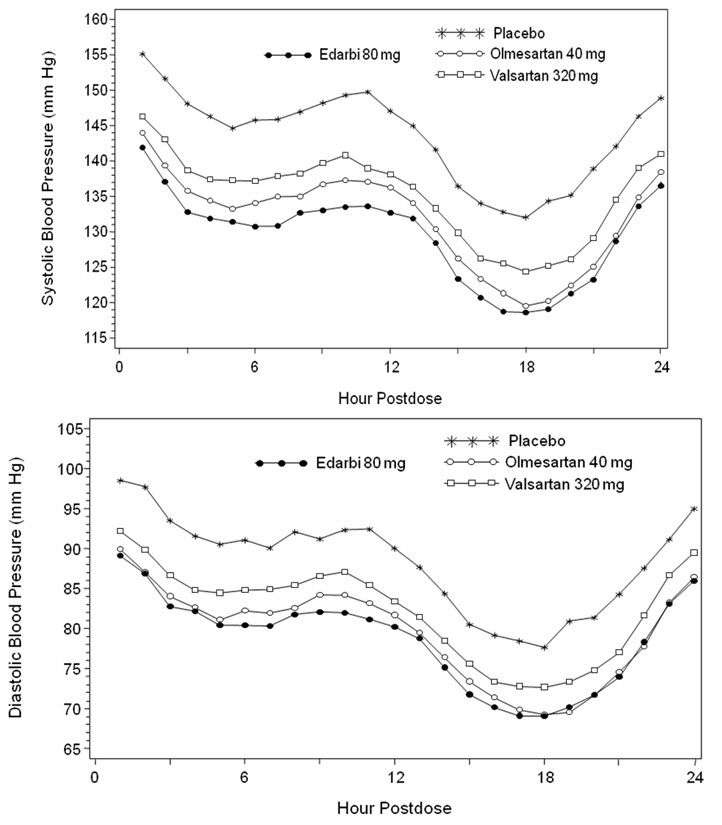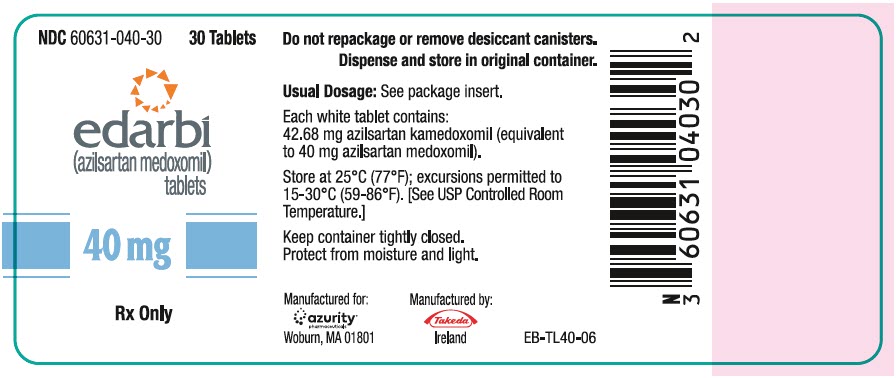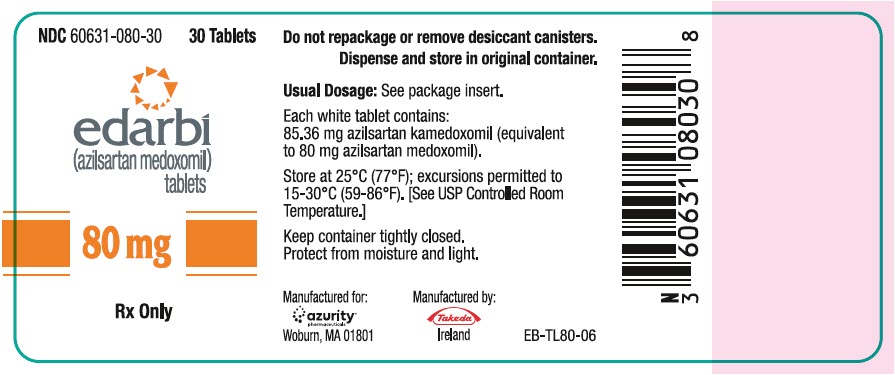 DRUG LABEL: Edarbi
NDC: 60631-040 | Form: TABLET
Manufacturer: Azurity Pharmaceuticals, Inc.
Category: prescription | Type: HUMAN PRESCRIPTION DRUG LABEL
Date: 20240123

ACTIVE INGREDIENTS: Azilsartan kamedoxomil 40 mg/1 1
INACTIVE INGREDIENTS: mannitol; fumaric acid; sodium hydroxide; HYDROXYPROPYL CELLULOSE (1600000 WAMW); croscarmellose sodium; MICROCRYSTALLINE CELLULOSE; magnesium stearate

HIGHLIGHTS OF PRESCRIBING INFORMATION

These HIGHLIGHTS do not include all the information needed to use EDARBI safely and effectively. See full prescribing information for EDARBI.
Edarbi (azilsartan medoxomil) tablets, for oral use
Initial U.S. Approval: 2011

WARNING: FETAL TOXICITY

See full prescribing information for complete boxed warning.

- When pregnancy is detected, discontinue Edarbi as soon as possible. (5.1, 8.1)
- Drugs that act directly on the renin-angiotensin system can cause injury and death to the developing fetus. (5.1, 8.1)

1 INDICATIONS AND USAGE

Edarbi is an angiotensin II receptor blocker indicated for the treatment of hypertension in adults, to lower blood pressure. Lowering blood pressure reduces the risk of fatal and nonfatal cardiovascular events, primarily strokes and myocardial infarctions. Edarbi may be used either alone or in combination with other antihypertensive agents. (1)

2 DOSAGE AND ADMINISTRATION

The recommended dose in adults is 80 mg taken once daily. Consider a starting dose of 40 mg for patients who are treated with high doses of diuretics. (2.1)

Edarbi may be administered with or without food. (2.1)

Edarbi may be administered with other antihypertensive agents. (2.1)

3 DOSAGE FORMS AND STRENGTHS

Tablets: 40 mg and 80 mg. (3)

4 CONTRAINDICATIONS

- Do not coadminister aliskiren-containing products with Edarbi in patients with diabetes. (4)

5 WARNINGS AND PRECAUTIONS

- Correct volume or salt depletion prior to administration of Edarbi. (5.2)
- Monitor for worsening renal function in patients with renal impairment. (5.3)

6 ADVERSE REACTIONS

The most common adverse reaction in adults was diarrhea (2%). (6.1)

To report SUSPECTED ADVERSE REACTIONS, contact Azurity Pharmaceuticals, Inc. at 1-800-461-7449 or FDA at 1-800-FDA-1088 or www.fda.gov/medwatch.

7 DRUG INTERACTIONS

Dual inhibition of the renin-angiotensin system: Increased risk of renal impairment, hypotension, and hyperkalemia. (7)

Lithium: Increases in serum lithium concentrations and lithium toxicity. (7)

8 USE IN SPECIFIC POPULATIONS

- Lactation: Breastfeeding is not recommended. (8.2)
- Geriatric Patients: Abnormally high serum creatinine values were more likely to be reported for patients age 75 or older. No overall difference in efficacy versus younger patients, but greater sensitivity of some older individuals cannot be ruled out. (8.5)
- In patients with an activated renin-angiotensin system, as by volume- or salt-depletion, renin-angiotensin-aldosterone system (RAAS) blockers such as azilsartan medoxomil can cause excessive hypotension. In susceptible patients, e.g., with renal artery stenosis, RAAS blockers can cause renal failure (5.2, 5.3).

FULL PRESCRIBING INFORMATION

WARNING: FETAL TOXICITY

- When pregnancy is detected, discontinue Edarbi as soon as possible [see Warnings and Precautions (5.1) and Use in Specific Populations (8.1)].
- Drugs that act directly on the renin-angiotensin system can cause injury and death to the developing fetus [see Warnings and Precautions (5.1) and Use in Specific Populations (8.1)].

1 INDICATIONS AND USAGE

Edarbi is indicated for the treatment of hypertension in adults, to lower blood pressure. Lowering blood pressure reduces the risk of fatal and nonfatal cardiovascular events, primarily strokes and myocardial infarctions. These benefits have been seen in controlled trials of antihypertensive drugs from a wide variety of pharmacologic classes, including the class to which this drug principally belongs. There are no controlled trials demonstrating risk reduction with Edarbi.

Control of high blood pressure should be part of comprehensive cardiovascular risk management, including, as appropriate, lipid control, diabetes management, antithrombotic therapy, smoking cessation, exercise, and limited sodium intake. Many patients will require more than one drug to achieve blood pressure goals. For specific advice on goals and management, see published guidelines, such as those of the National High Blood Pressure Education Program's Joint National Committee on Prevention, Detection, Evaluation, and Treatment of High Blood Pressure (JNC).

Numerous antihypertensive drugs, from a variety of pharmacologic classes and with different mechanisms of action, have been shown in randomized controlled trials to reduce cardiovascular morbidity and mortality, and it can be concluded that it is blood pressure reduction, and not some other pharmacologic property of the drugs, that is largely responsible for those benefits. The largest and most consistent cardiovascular outcome benefit has been a reduction in the risk of stroke, but reductions in myocardial infarction and cardiovascular mortality also have been seen regularly.

Elevated systolic or diastolic pressure causes increased cardiovascular risk, and the absolute risk increase per mmHg is greater at higher blood pressures, so that even modest reductions of severe hypertension can provide substantial benefit. Relative risk reduction from blood pressure reduction is similar across populations with varying absolute risk, so the absolute benefit is greater in patients who are at higher risk independent of their hypertension (for example, patients with diabetes or hyperlipidemia), and such patients would be expected to benefit from more aggressive treatment to a lower blood pressure goal.

Some antihypertensive drugs have smaller blood pressure effects (as monotherapy) in black patients, and many antihypertensive drugs have additional approved indications and effects (e.g., on angina, heart failure, or diabetic kidney disease). These considerations may guide selection of therapy.

Edarbi may be used alone or in combination with other antihypertensive agents.

2 DOSAGE AND ADMINISTRATION

2.1 Recommended Dose

The recommended dose in adults is 80 mg taken orally once daily. Consider a starting dose of 40 mg for patients who are treated with high doses of diuretics.

2.2 Handling Instructions

Do not repackage Edarbi. Dispense and store Edarbi in its original container to protect Edarbi from light and moisture.

3 DOSAGE FORMS AND STRENGTHS

Edarbi is supplied as white to nearly white round tablets in the following dosage strengths:

- 40-mg tablets – debossed "ASL" on one side and "40" on the other
- 80-mg tablets – debossed "ASL" on one side and "80" on the other

4 CONTRAINDICATIONS

Do not coadminister aliskiren-containing products with Edarbi in patients with diabetes [see Drug Interactions (7)].

5 WARNINGS AND PRECAUTIONS

5.1 Fetal Toxicity

Edarbi can cause fetal harm when administered to a pregnant woman. Use of drugs that act on the renin-angiotensin system during the second and third trimesters of pregnancy reduces fetal renal function and increases fetal and neonatal morbidity and death. Resulting oligohydramnios can be associated with fetal lung hypoplasia and skeletal deformations. Potential neonatal adverse effects include skull hypoplasia, anuria, hypotension, renal failure, and death. When pregnancy is detected, discontinue Edarbi as soon as possible [see Use in Specific Populations (8.1)].

5.2 Hypotension in Volume- or Salt-Depleted Patients

In patients with an activated renin-angiotensin system, such as volume- and/or salt-depleted patients (e.g., those being treated with high doses of diuretics), symptomatic hypotension may occur after initiation of treatment with Edarbi. Correct volume or salt depletion prior to administration of Edarbi, or start treatment at 40 mg. If hypotension does occur, the patient should be placed in the supine position and, if necessary, given an intravenous infusion of normal saline. A transient hypotensive response is not a contraindication to further treatment, which usually can be continued without difficulty once the blood pressure has stabilized.

5.3 Impaired Renal Function

As a consequence of inhibiting the renin-angiotensin system, changes in renal function may be anticipated in susceptible individuals treated with Edarbi. In patients whose renal function may depend on the activity of the renin-angiotensin system (e.g., patients with severe congestive heart failure, renal artery stenosis, or volume depletion), treatment with angiotensin-converting enzyme inhibitors and angiotensin receptor blockers has been associated with oliguria or progressive azotemia and rarely with acute renal failure and death. Similar results may be anticipated in patients treated with Edarbi [see Drug Interactions (7), Use in Specific Populations (8.6), and Clinical Pharmacology (12.3)].

In studies of ACE inhibitors in patients with unilateral or bilateral renal artery stenosis, increases in serum creatinine or blood urea nitrogen have been reported. There has been no long-term use of Edarbi in patients with unilateral or bilateral renal artery stenosis, but similar results may be expected.

6 ADVERSE REACTIONS

6.1 Clinical Trials Experience

Because clinical trials are conducted under widely varying conditions, adverse reaction rates observed in the clinical trials of a drug cannot be directly compared to rates in the clinical trials of another drug and may not reflect the rates observed in practice.

A total of 4814 patients were evaluated for safety when treated with Edarbi at doses of 20, 40, or 80 mg in clinical trials. This includes 1704 patients treated for at least six months; of these, 588 were treated for at least one year.

Treatment with Edarbi was well-tolerated with an overall incidence of adverse reactions similar to placebo. The rate of withdrawals due to adverse events in placebo-controlled monotherapy and combination therapy trials was 2.4% (19/801) for placebo, 2.2% (24/1072) for Edarbi 40 mg, and 2.7% (29/1074) for Edarbi 80 mg. The most common adverse event leading to discontinuation, hypotension/orthostatic hypotension, was reported by 0.4% (8/2146) patients randomized to Edarbi 40 mg or 80 mg compared to 0% (0/801) patients randomized to placebo. Generally, adverse reactions were mild, not dose related, and similar regardless of age, gender, and race.

In placebo-controlled monotherapy trials, diarrhea was reported up to 2% in patients treated with Edarbi 80 mg daily compared with 0.5% of patients on placebo.

Other adverse reactions with a plausible relationship to treatment that have been reported with an incidence of ≥0.3% and greater than placebo in more than 3300 patients treated with Edarbi in controlled trials are listed below:

Gastrointestinal Disorders: nausea
General Disorders and Administration Site Conditions: asthenia, fatigue
Musculoskeletal and Connective Tissue Disorders: muscle spasm
Nervous System Disorders: dizziness, dizziness postural
Respiratory, Thoracic, and Mediastinal Disorders: cough

6.2 Postmarketing Experience

The following adverse reactions have been identified during the postmarketing use of EDARBI. Because these reactions are reported voluntarily from a population of uncertain size, it is not always possible to reliably estimate their frequency or establish a causal relationship to drug exposure.

- Rash
- Pruritus
- Angioedema

7 DRUG INTERACTIONS

7.1 Non-steroidal Anti-Inflammatory Agents, including Selective Cyclooxygenase-2 Inhibitors (COX-2 Inhibitors)

In patients who are elderly, volume-depleted (including those on diuretic therapy), or who have compromised renal function, coadministration of NSAIDs, including selective COX-2 inhibitors, with angiotensin II receptor antagonists, including azilsartan, may result in deterioration of renal function, including possible acute renal failure. These effects are usually reversible. Monitor renal function periodically in patients receiving azilsartan and NSAID therapy.

The antihypertensive effect of angiotensin II receptor antagonists, including azilsartan, may be attenuated by NSAIDs, including selective COX-2 inhibitors.

7.2 Dual Blockade of the Renin-Angiotensin System (RAS)

Dual blockade of the RAS with angiotensin receptor blockers, ACE inhibitors, or aliskiren is associated with increased risks of hypotension, hyperkalemia, and changes in renal function (including acute renal failure) compared to monotherapy. Most patients receiving the combination of two RAS inhibitors do not obtain any additional benefit compared to monotherapy. In general, avoid combined use of RAS inhibitors. Closely monitor blood pressure, renal function and electrolytes in patients on Edarbi and other agents that affect the RAS.

Do not coadminister aliskiren with Edarbi in patients with diabetes. Avoid use of aliskiren with Edarbi in patients with renal impairment (GFR <60 mL/min).

7.3 Lithium

Increases in serum lithium concentrations and lithium toxicity have been reported during concomitant administration of lithium with angiotensin II receptor agonists. Monitor serum lithium levels during concomitant use.

8 USE IN SPECIFIC POPULATIONS

8.1 Pregnancy

Risk Summary

Edarbi can cause fetal harm when administered to a pregnant woman. Use of drugs that act on the renin-angiotensin system during the second and third trimesters of pregnancy reduces fetal renal function and increases fetal and neonatal morbidity and death (see Clinical Considerations). Most epidemiologic studies examining fetal abnormalities after exposure to antihypertensive use in the first trimester have not distinguished drugs affecting the renin-angiotensin system from other antihypertensive agents.

When pregnancy is detected, discontinue Edarbi as soon as possible.

The estimated background risk of major birth defects and miscarriage for the indicated population is unknown. All pregnancies have a background risk of birth defect, loss, or other adverse outcomes. In the U.S. general population, the estimated background risk of major birth defects and miscarriage in clinically recognized pregnancies is 2-4% and 15-20%, respectively.

Clinical Considerations

Disease-associated maternal and/or embryo/fetal risk

Hypertension in pregnancy increases the maternal risk for pre-eclampsia, gestational diabetes, premature delivery, and delivery complications (e.g., need for cesarean section, and post-partum hemorrhage). Hypertension increases the fetal risk for intrauterine growth restriction and intrauterine death. Pregnant women with hypertension should be carefully monitored and managed accordingly.

Fetal/Neonatal adverse reactions

Oligohydramnios in pregnant women who use drugs affecting the renin-angiotensin system in the second and third trimesters can result in the following: reduced fetal renal function leading to anuria and renal failure, fetal lung hypoplasia, skeletal deformations, including skull hypoplasia, hypotension and death.

Perform serial ultrasound examinations to assess the intra-amniotic environment. Fetal testing may be appropriate, based on the week of pregnancy. Patients and physicians should be aware, however, that oligohydramnios may not appear until after the fetus has sustained irreversible injury.

Closely observe infants with histories of in utero exposure to Edarbi for hypotension, oliguria, and hyperkalemia. In neonates with a history of in utero exposure to Edarbi, if oliguria or hypotension occurs, support blood pressure and renal perfusion. Exchange transfusions or dialysis may be required as a means of reversing hypotension and/or substituting for disordered renal function.

Data

Animal Data

In peri- and postnatal rat development studies, adverse effects on pup viability, delayed incisor eruption and dilatation of the renal pelvis along with hydronephrosis were seen when azilsartan medoxomil was administered to pregnant and nursing rats at 1.2 times the MRHD on a mg/m^2 basis. Reproductive toxicity studies indicated that azilsartan medoxomil was not teratogenic when administered at oral doses up to 1000 mg azilsartan medoxomil/kg/day to pregnant rats (122 times the MRHD on a mg/m^2 basis) or up to 50 mg azilsartan medoxomil/kg/day to pregnant rabbits (12 times the MRHD on a mg/m^2 basis). M-II also was not teratogenic in rats or rabbits at doses up to 3000 mg M-II/kg/day. Azilsartan crossed the placenta and was found in the fetuses of pregnant rats and was excreted into the milk of lactating rats.

8.2 Lactation

Risk Summary

There is limited information regarding the presence of azilsartan in human milk, the effects on the breastfed infant, or the effects on milk production. Azilsartan is present in rat milk. Because of the potential for adverse effects on the nursing infant, advise a nursing woman that breastfeeding is not recommended during treatment with Edarbi.

8.4 Pediatric Use

Safety and effectiveness in pediatric patients have not been established.

Use of Edarbi is not recommended in children less than 2 years of age. It is not known whether post-natal use of azilsartan in patients less than 2 years of age, before maturation of kidney function is complete, has a long-term deleterious effect on the kidney.

Juvenile Animal Studies

In juvenile rat studies, dosing with azilsartan starting on post-natal day 14 (equivalent to a neonate with morphologically and functionally immature kidneys) resulted in increased incidence of edema of the renal papilla at the end of 4-week recovery period that was non-reversible. These findings occurred in the high-dose group (10 mg/kg) and were not observed in juvenile rats dosed starting on post-natal day 21 (equivalent to a human approximately 2 years of age) or adult rats.

8.5 Geriatric Use

No dose adjustment with Edarbi is necessary in elderly patients. Of the total patients in clinical studies with Edarbi, 26% were elderly (65 years of age and older); 5% were 75 years of age and older. Abnormally high serum creatinine values were more likely to be reported for patients age 75 or older. No other differences in safety or effectiveness were observed between elderly patients and younger patients, but greater sensitivity of some older individuals cannot be ruled out [see Clinical Pharmacology (12.3)].

8.6 Renal Impairment

Dose adjustment is not required in patients with mild-to-severe renal impairment or end-stage renal disease. Patients with moderate to severe renal impairment are more likely to report abnormally high serum creatinine values.

8.7 Hepatic Impairment

No dose adjustment is necessary for subjects with mild or moderate hepatic impairment. Edarbi has not been studied in patients with severe hepatic impairment [see Clinical Pharmacology (12.3)].

10 OVERDOSAGE

Limited data are available related to overdosage in humans. During controlled clinical trials in healthy subjects, once-daily doses up to 320 mg of Edarbi were administered for seven days and were well tolerated. In the event of an overdose, supportive therapy should be instituted as dictated by the patient's clinical status. Azilsartan is not dialyzable [see Clinical Pharmacology (12.3)].

11 DESCRIPTION

Edarbi (azilsartan medoxomil), a prodrug, is hydrolyzed to azilsartan in the gastrointestinal tract during absorption. Azilsartan is an angiotensin II receptor blocker.

The drug substance used in the drug product formulation is the potassium salt of azilsartan medoxomil, also known by the US accepted name of azilsartan kamedoxomil and is chemically described as (5-Methyl-2-oxo-1,3-dioxol-4-yl)methyl 2-ethoxy-1-{[2'-(5-oxo-4,5-dihydro-1,2,4-oxadiazol-3-yl)biphenyl-4-yl]methyl}-1H-benzimidazole-7-carboxylate monopotassium salt.

Its empirical formula is C30H23KN4O8 and its structural formula is:

Azilsartan kamedoxomil is a white to nearly white powder with a molecular weight of 606.62. It is practically insoluble in water and freely soluble in methanol.

Edarbi is available for oral use as tablets. The tablets have a characteristic odor. Each Edarbi tablet contains 42.68 or 85.36 mg of azilsartan kamedoxomil, which is equivalent to containing 40 mg or 80 mg respectively, of azilsartan medoxomil and the following inactive ingredients: mannitol, fumaric acid, sodium hydroxide, hydroxypropyl cellulose, croscarmellose sodium, microcrystalline cellulose, and magnesium stearate.

12 CLINICAL PHARMACOLOGY

12.1 Mechanism of Action

Angiotensin II is formed from angiotensin I in a reaction catalyzed by angiotensin-converting enzymes (ACE, kinase II). Angiotensin II is the principal pressor agent of the renin-angiotensin system, with effects that include vasoconstriction, stimulation of synthesis and release of aldosterone, cardiac stimulation, and renal reabsorption of sodium. Azilsartan medoxomil is an orally administered prodrug that is rapidly converted by esterases during absorption to the active moiety, azilsartan. Azilsartan blocks the vasoconstrictor and aldosterone-secreting effects of angiotensin II by selectively blocking the binding of angiotensin II to the AT1 receptor in many tissues, such as vascular smooth muscle and the adrenal gland. Its action is, therefore, independent of the pathway for angiotensin II synthesis.

An AT2 receptor is also found in many tissues, but this receptor is not known to be associated with cardiovascular homeostasis. Azilsartan has more than a 10,000-fold greater affinity for the AT1 receptor than for the AT2 receptor.

Blockade of the renin-angiotensin system with ACE inhibitors, which inhibit the biosynthesis of angiotensin II from angiotensin I, is widely used in the treatment of hypertension. ACE inhibitors also inhibit the degradation of bradykinin, a reaction catalyzed by ACE. Because azilsartan does not inhibit ACE (kinase II), it should not affect bradykinin levels. Whether this difference has clinical relevance is not yet known. Azilsartan does not bind to or block other receptors or ion channels known to be important in cardiovascular regulation.

Blockade of the angiotensin II receptor inhibits the negative regulatory feedback of angiotensin II on renin secretion, but the resulting increased plasma renin activity and angiotensin II circulating levels do not overcome the effect of azilsartan on blood pressure.

12.2 Pharmacodynamics

Azilsartan inhibits the pressor effects of an angiotensin II infusion in a dose-related manner. An azilsartan single dose equivalent to 32 mg azilsartan medoxomil inhibited the maximal pressor effect by approximately 90% at peak, and approximately 60% at 24 hours. Plasma angiotensin I and II concentrations and plasma renin activity increased while plasma aldosterone concentrations decreased after single and repeated administration of Edarbi to healthy subjects; no clinically significant effects on serum potassium or sodium were observed.

Effect on Cardiac Repolarization

A thorough QT/QTc study was conducted to assess the potential of azilsartan to prolong the QT/QTc interval in healthy subjects. There was no evidence of QT/QTc prolongation at a dose of 320 mg of Edarbi.

12.3 Pharmacokinetics

Absorption

Azilsartan medoxomil is hydrolyzed to azilsartan, the active metabolite, in the gastrointestinal tract during absorption. Azilsartan medoxomil is not detected in plasma after oral administration. Dose proportionality in exposure was established for azilsartan in the azilsartan medoxomil dose range of 20 mg to 320 mg after single or multiple dosing.

The estimated absolute bioavailability of azilsartan following administration of azilsartan medoxomil is approximately 60%. After oral administration of azilsartan medoxomil, peak plasma concentrations (Cmax) of azilsartan are reached within 1.5 to 3 hours. Food does not affect the bioavailability of azilsartan.

Distribution

The volume of distribution of azilsartan is approximately 16 L. Azilsartan is highly bound to human plasma proteins (>99%), mainly serum albumin. Protein binding is constant at azilsartan plasma concentrations well above the range achieved with recommended doses.

In rats, minimal azilsartan-associated radioactivity crossed the blood-brain barrier. Azilsartan passed across the placental barrier in pregnant rats and was distributed to the fetus.

Metabolism and Elimination

Azilsartan is metabolized to two primary metabolites. The major metabolite in plasma is formed by O-dealkylation, referred to as metabolite M-II, and the minor metabolite is formed by decarboxylation, referred to as metabolite M-I. Systemic exposures to the major and minor metabolites in humans were approximately 50% and less than 1% of azilsartan, respectively. M-I and M-II do not contribute to the pharmacologic activity of Edarbi. The major enzyme responsible for azilsartan metabolism is CYP2C9.

Following an oral dose of ^14C-labeled azilsartan medoxomil, approximately 55% of radioactivity was recovered in feces and approximately 42% in urine, with 15% of the dose excreted in urine as azilsartan. The elimination half-life of azilsartan is approximately 11 hours and renal clearance is approximately 2.3 mL/min. Steady-state levels of azilsartan are achieved within five days, and no accumulation in plasma occurs with repeated once-daily dosing.

Specific Populations

The effect of demographic and functional factors on the pharmacokinetics of azilsartan was studied in single and multiple dose studies. Pharmacokinetic measures indicating the magnitude of the effect on azilsartan are presented in Figure 1 as change relative to reference (test/reference). Effects are modest and do not call for dosage adjustment.

Figure 1. Impact of intrinsic factors on the pharmacokinetics of azilsartan

Drug Interactions

No clinically significant drug interactions have been observed in studies of azilsartan medoxomil or azilsartan given with amlodipine, antacids, chlorthalidone, digoxin, fluconazole, glyburide, ketoconazole, metformin, pioglitazone, and warfarin. Therefore, Edarbi may be used concomitantly with these medications.

13 NONCLINICAL TOXICOLOGY

13.1 Carcinogenesis, Mutagenesis, Impairment of Fertility

Carcinogenesis

Azilsartan medoxomil was not carcinogenic when assessed in 26-week transgenic (Tg.rasH2) mouse and two-year rat studies. The highest doses tested (450 mg azilsartan medoxomil/kg/day in the mouse and 600 mg azilsartan medoxomil/kg/day in the rat) produced exposures to azilsartan that are 12 (mice) and 27 (rats) times the average exposure to azilsartan in humans given the maximum recommended human dose (MRHD, 80 mg azilsartan medoxomil/day). M-II was not carcinogenic when assessed in 26-week Tg.rasH2 mouse and two-year rat studies. The highest doses tested (approximately 8000 mg M-II/kg/day [males] and 11,000 mg M-II/kg/day [females] in the mouse and 1000 mg M-II/kg/day [males] and up to 3000 mg M-II/kg/day [females] in the rat) produced exposures that are, on average, about 30 (mice) and seven (rats) times the average exposure to M-II in humans at the MRHD.

Mutagenesis

Azilsartan medoxomil, azilsartan, and M-II were positive for structural aberrations in the Chinese Hamster Lung Cytogenetic Assay. In this assay, structural chromosomal aberrations were observed with the prodrug, azilsartan medoxomil, without metabolic activation. The active moiety, azilsartan was also positive in this assay both with and without metabolic activation. The major human metabolite, M-II was also positive in this assay during a 24-hour assay without metabolic activation.

Azilsartan medoxomil, azilsartan, and M-II were devoid of genotoxic potential in the Ames reverse mutation assay with Salmonella typhimurium and Escherichia coli, the in vitro Chinese Hamster Ovary Cell forward mutation assay, the in vitro mouse lymphoma (tk) gene mutation test, the ex vivo unscheduled DNA synthesis test, and the in vivo mouse and/or rat bone marrow micronucleus assay.

Impairment of Fertility

There was no effect of azilsartan medoxomil on the fertility of male or female rats at oral doses of up to 1000 mg azilsartan medoxomil/kg/day (6000 mg/m^2 [approximately 122 times the MRHD of 80 mg azilsartan medoxomil/60 kg on a mg/m^2 basis]). Fertility of rats also was unaffected at doses of up to 3000 mg M-II/kg/day.

14 CLINICAL STUDIES

The antihypertensive effects of Edarbi have been demonstrated in a total of seven double-blind, randomized studies, which included five placebo-controlled and four active comparator-controlled studies (not mutually exclusive). The studies ranged from six weeks to six months in duration, at doses ranging from 20 mg to 80 mg once daily. A total of 5941 patients (3672 given Edarbi, 801 given placebo, and 1468 given active comparator) with mild, moderate or severe hypertension were studied. Overall, 51% of patients were male and 26% were 65 years or older; 67% were white and 19% were black.

Two 6-week, randomized, double-blind studies compared the effect on blood pressure of Edarbi at doses of 40 mg and 80 mg, with placebo and with active comparators. Blood pressure reductions compared to placebo based on clinic blood pressure measurements at trough and 24-hour mean blood pressure by ambulatory blood pressure monitoring (ABPM) are shown in Table 1 for both studies. Edarbi, 80 mg, was statistically superior to placebo and active comparators for both clinic and 24-hour mean blood pressure measurements.

Table 1. Placebo Corrected Mean Change from Baseline in Systolic/Diastolic Blood Pressure at 6 Weeks (mm Hg)
 | Study 1 N=1285 |  | Study 2 N=989
 | Clinic Blood Pressure (Mean Baseline 157.4/92.5) | 24 Hour Mean by ABPM (Mean Baseline 144.9/88.7) | Clinic Blood Pressure (Mean Baseline 159.0/91.8) | 24 Hour Mean by ABPM (Mean Baseline 146.2/87.6)
Edarbi 40 mg | -14.6/-6.2 | -13.2/-8.6 | -12.4/-7.1 | -12.1/-7.7
Edarbi 80 mg | -14.9/-7.5 | -14.3/-9.4 | -15.5/-8.6 | -13.2/-7.9
Olmesartan 40 mg | -11.4/-5.3 | -11.7/-7.7 | -12.8/-7.1 | -11.2/-7.0
Valsartan 320 mg | -9.5/-4.4 | -10.0/-7.0

In a study comparing Edarbi to valsartan over 24 weeks, similar results were observed.

Most of the antihypertensive effect occurs within the first two weeks of dosing.

Figure 2 shows the 24-hour ambulatory systolic and diastolic blood pressure profiles at endpoint.

Figure 2. Mean Ambulatory Blood Pressure at 6 Weeks by Dose and Hour

Other studies showed similar 24-hour ambulatory blood pressure profiles.

Edarbi has a sustained and consistent antihypertensive effect during long-term treatment, as shown in a study that randomized patients to placebo or continued Edarbi after 26 weeks. No rebound effect was observed following the abrupt cessation of Edarbi therapy.

Edarbi was effective in reducing blood pressure regardless of the age, gender, or race of patients, but the effect, as monotherapy, was smaller, approximately half, in black patients, who tend to have low renin levels. This has been generally true for other angiotensin II antagonists and ACE inhibitors.

Edarbi has about its usual blood pressure lowering effect size when added to a calcium channel blocker (amlodipine) or a thiazide-type diuretic (chlorthalidone).

There are no trials of Edarbi demonstrating reductions in cardiovascular risk in patients with hypertension, but at least one pharmacologically similar drug has demonstrated such benefits.

16 HOW SUPPLIED/STORAGE AND HANDLING

Edarbi tablets are unscored and white to nearly white, debossed with "ASL" on one side and "40" or "80" on the other.

Tablet | NDC 60631-xxx-xx
Tablet | Bottle/30
40 mg | 040-30
80 mg | 080-30

Storage

Store at 25°C (77°F); excursions permitted to 15°-30°C (59°-86°F) [see USP Controlled Room Temperature]. Keep container tightly closed. Protect from moisture and light. Do not repackage; dispense and store in original container.

17 PATIENT COUNSELING INFORMATION

Advise the patient to read the FDA-approved patient labeling (Patient Information)

Pregnancy

Tell female patients of childbearing potential about the consequences of exposure to Edarbi during pregnancy. Discuss treatment options with women planning to become pregnant. Tell patients to report pregnancies to their physicians as soon as possible.

Patient Information
Edarbi (eh-DAR-bee)
(azilsartan medoxomil)
Tablets

Read this Patient Information leaflet before you start taking Edarbi and each time you get a refill. There may be new information. This information does not take the place of talking to your doctor about your medical condition or your treatment.

What is the most important information I should know about Edarbi?

- Edarbi can cause harm or death to your unborn baby.
- Talk to your doctor about other ways to lower your blood pressure if you plan to become pregnant.
- If you become pregnant while taking Edarbi, tell your doctor right away. Your doctor may switch you to a different medicine to treat your high blood pressure.

What is Edarbi?

Edarbi is a prescription medicine called an angiotensin II receptor blocker (ARB) used to treat high blood pressure (hypertension) in adults.

Your doctor may prescribe other medicines for you to take along with Edarbi to treat your high blood pressure.

It is not known if Edarbi is safe and effective in children under 18 years of age.

What should I tell my doctor before taking Edarbi?

Before you take Edarbi, tell your doctor if you:

- have been told that you have abnormal body salt (electrolytes) levels in your blood
- are pregnant or plan to become pregnant. See "What is the most important information I should know about Edarbi?"
- are breastfeeding or plan to breastfeed. It is not known if Edarbi passes into your breast milk. You and your doctor should decide if you will take Edarbi or breastfeed. You should not do both. Talk with your doctor about the best way to feed your baby if you take Edarbi.

Tell your doctor about all the medicines you take, including prescription and nonprescription medicines, vitamins, and herbal supplements.

Especially tell your doctor if you take:

- other medicines used to treat your high blood pressure or heart problem
- water pills (diuretic)

Ask your doctor if you are not sure if you are taking a medicine listed above.

Know the medicines you take. Keep a list of them and show it to your doctor or pharmacist when you get a new medicine.

How should I take Edarbi?

- Your doctor will tell you how much Edarbi to take and when to take it. Follow his/her instructions.
- Edarbi can be taken with or without food.
- If you take too much Edarbi, call your doctor or go to the nearest hospital emergency room right away.

What are the possible side effects of Edarbi?
Edarbi may cause side effects, including:

- Harm or death to your unborn fetus if taken in the second or third trimester. See "What is the most important information I should know about Edarbi?"
- Low blood pressure (hypotension) and dizziness is most likely to happen if you also:
  - take water pills (diuretics)
  - are on a low-salt diet
  - take other medicines that affect your blood pressure
  - get sick with vomiting or diarrhea
  - do not drink enough fluids

If you feel faint or dizzy, lie down and call your doctor right away.

These are not all the possible side effects with Edarbi. Tell your doctor if you have any side effect that bothers you or that does not go away.

Call your doctor for medical advice about side effects. You may report side effects to FDA at 1-800-FDA-1088.

How do I store Edarbi?

- Store Edarbi at 59°F to 86°F (15°C to 30°C).
- Store Edarbi in the original container that you received from your pharmacist or doctor. Do not put Edarbi into a different container.
- Keep Edarbi in a tightly closed container, and keep Edarbi out of the light.

Keep Edarbi and all medicines out of the reach of children.

General information about Edarbi.

Medicines are sometimes prescribed for purposes other than those listed in a Patient Information leaflet. Do not give Edarbi to other people, even if they have the same symptoms you have. It may harm them.

This Patient Information leaflet summarizes the most important information about Edarbi. If you would like more information, talk with your doctor. You can ask your pharmacist or doctor for information about Edarbi that is written for health professionals.

For more information, go to www.edarbi.com or call 1-800-461-7449.

What is high blood pressure (hypertension)?

Blood pressure is the force in your blood vessels when your heart beats and when your heart rests. You have high blood pressure when the force is too great.

High blood pressure makes the heart work harder to pump blood through the body and causes damage to the blood vessels. Edarbi tablets can help your blood vessels relax so your blood pressure is lower. Medicines that lower your blood pressure may lower your chance of having a stroke or heart attack.

What are the ingredients in Edarbi?

Active ingredient: azilsartan medoxomil

Inactive ingredients: mannitol, fumaric acid, sodium hydroxide, hydroxypropyl cellulose, croscarmellose sodium, microcrystalline cellulose, and magnesium stearate.

Manufactured by:
Takeda
Ireland

Manufactured for:
azurity®
pharmaceuticals
Woburn, MA 01801

Patent: https://azurity.com/patents_and_trademarks/

This product's labeling may have been updated. For current Full Prescribing Information, please visit www.edarbi.com

Edarbi is a trademark of Takeda Pharmaceutical Company Limited registered with the U.S. Patent and Trademark Office and used under license by Azurity Pharmaceuticals, Inc.

EB-PI-09 Rev. Jan2024

PRINCIPAL DISPLAY PANEL - 40 mg Tablet Bottle Label

NDC 60631-040-30
30 Tablets

edarbi
(azilsartan medoxomil)
tablets

40 mg

Rx Only

PRINCIPAL DISPLAY PANEL - 80 mg Tablet Bottle Label

NDC 60631-080-30
30 Tablets

edarbi
(azilsartan medoxomil)
tablets

80 mg

Rx Only